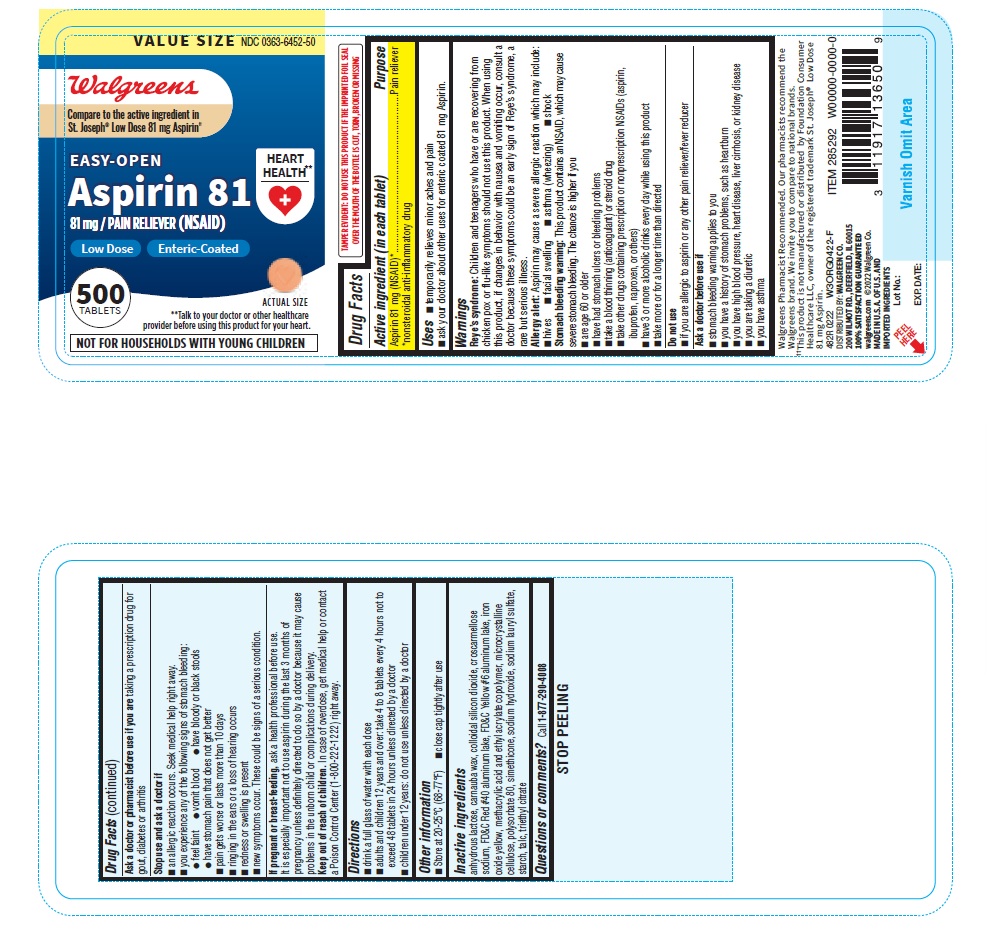 DRUG LABEL: Aspirin 81
NDC: 0363-6452 | Form: TABLET
Manufacturer: WALGREENS
Category: otc | Type: HUMAN OTC DRUG LABEL
Date: 20250130

ACTIVE INGREDIENTS: ASPIRIN 81 mg/1 1
INACTIVE INGREDIENTS: SILICON DIOXIDE; DIMETHICONE; STARCH, CORN; FD&C YELLOW NO. 6 ALUMINUM LAKE; ANHYDROUS LACTOSE; CARNAUBA WAX; CROSCARMELLOSE SODIUM; POLYSORBATE 80; TRIETHYL CITRATE; FD&C RED NO. 40 ALUMINUM LAKE; METHACRYLIC ACID AND ETHYL ACRYLATE COPOLYMER; SODIUM HYDROXIDE; SODIUM LAURYL SULFATE; TALC; MICROCRYSTALLINE CELLULOSE; FERRIC OXIDE YELLOW

482R Walgreens 0363-6452 Aspirin 81 mg 500s

Active ingredient (in each tablet)
Aspirin 81 mg (NSAID)*
*nonsteroidal anti-inflammatory drug

Purpose
Pain reliever

Uses

• temporarily relieves minor aches and pains

• ask your doctor about other uses for enteric coated 81 mg Aspirin.

Warnings
Reye’s syndrome: Children and teenagers who have or are recovering from chicken pox or flu-like symptoms should not use this product. When using this product, if changes in behavior with nausea and vomiting occur, consult a doctor because these symptoms could be an early sign of Reye’s syndrome, a rare but serious illness.

Allergy alert: Aspirin may cause a severe allergic reaction which may include: •hives • facial swelling • asthma (wheezing) • shock

Stomach bleeding warning: This product contains an NSAID, which may cause severe stomach bleeding. The chance is higher if you
• are age 60 or older
• have had stomach ulcers or bleeding problems
• take a blood thinning (anticoagulant) or steroid drug
• take other drugs containing prescription or nonprescription NSAIDs (aspirin, ibuprofen, naproxen, or others)
• have 3 or more alcoholic drinks every day while using this product
• take more or for a longer time than directed

Do not use

- if you have ever had an allergic reaction to any other pain reliever/fever reducer.

Ask a doctor before use if

- stomach bleeding warning applies to you
- you have a history of stomach problems such as heartburn
- you have high blood pressure, heart disease, liver cirrhosis, or kidney disease
- you are taking a diuretic
- you have asthma

Ask a doctor or pharmacist before use if you are taking a prescription drug for diabetes, gout, or arthritis.

Stop use and ask a doctor if

- you experience any of the following signs of stomach bleeding:
- feel faint
- vomit blood
- have bloody or black stools
- have stomach pain that does not get better
- an allergic reaction occurs

Seek medical help right away if

- new symptoms occur
- ringing in the ears or loss of hearing occurs
- redness or swelling is present
- pain gets worse or lasts more than 10 days
- fever gets worse or lasts more than 3 days

PREGNANCY OR BREAST FEEDING

If pregnant or breast-feeding, ask a health professional before use. It is especially important not to use aspirin at 20 weeks or later in pregnancy unless definitely directed to do so by a doctor because it may cause problems in the unborn child or complications during delivery.

Keep out of reach of children.

Overdose warning: In case of overdose, get medical help or contact a Poison Control Center (1-800-222-1222) right away.

Directions

- drink a full glass of water with each dose
- adults and children 12 years and over: take 4 to 8 tablets every 4 hours not to exceed 48 tablets in 24 hours unless directed by a doctor
- children under 12 years: do not use unless directed by a doctor

Other information

- Store at 20-25°C (68-77°F)
- close cap tightly after use

Inactive ingredients

anhydrous lactose, carnauba wax, colloidal silicon dioxide, croscarmellose sodium, FD&C red #40 aluminum lake, FD&C yellow #6 aluminum lake, iron oxide yellow, methacrylic acid and ethyl acrylate copolymer, microcrystalline cellulose, polysorbate 80, simethicone, sodium hydroxide, sodium lauryl sulfate, starch, talc, triethyl citrate

Questions or comments? Call 1-877-290-4008